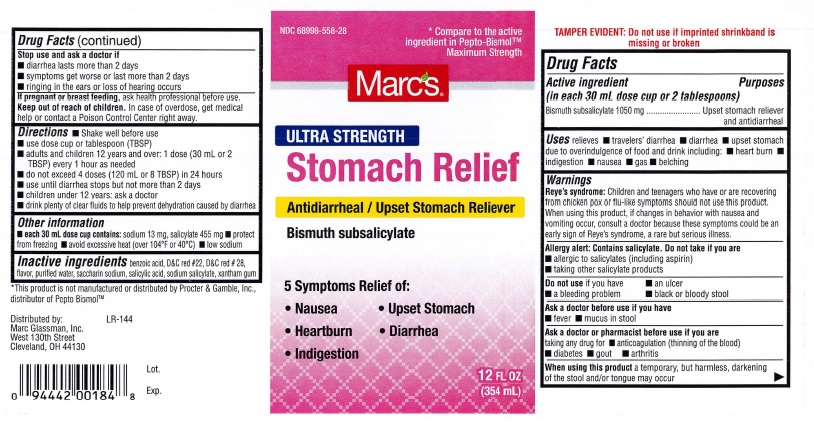 DRUG LABEL: Stomach Relief, Ultra Strength
NDC: 68998-558 | Form: SUSPENSION
Manufacturer: Marc Glassman, Inc.
Category: otc | Type: HUMAN OTC DRUG LABEL
Date: 20251226

ACTIVE INGREDIENTS: BISMUTH SUBSALICYLATE 1050 mg/30 mL
INACTIVE INGREDIENTS: BENZOIC ACID; D&C RED NO. 22; D&C RED NO. 28; WATER; SACCHARIN SODIUM; SALICYLIC ACID; SODIUM SALICYLATE; XANTHAN GUM

Stomach Relief, Ultra Strength

Drug Facts

Active ingredient
(in each 30 mL dose cup or 2 tablespoons)
Bismuth subsalicylate 1050 mg

Purposes
Bismuth subsalicylate ....................... Upset stomach reliever
and antidiarrheal

INDICATIONS AND USAGE

Uses relieves ■ travelers' diarrhea ■ diarrhea ■ upset stomach
due to overindulgence of food and drink including: ■ heart burn ■
indigestion ■ nausea ■ gas ■ belching

Warnings
Reye's syndrome: Children and teenagers who have or are recovering
from chicken pox or flu-like symptoms should not use this product.
When using this product, if changes in behavior with nausea and
vomiting occur, consult a doctor because these symptoms could be an
early sign of Reye's syndrome, a rare but serious illness.

Allergy alert: Contains salicylate. Do not take if you are
■ allergic to salicylates (including aspirin)
■ taking other salicylate products

Do not use if you have ■ an ulcer
■ a bleeding problem ■ black or bloody stool

Ask a doctor before use if you have
■ fever ■ mucus in stool

Ask a doctor or pharmacist before use if you are
taking any drug for ■ anticoagulation (thinning of the blood)
■ diabetes ■ gout ■ arthritis

When using this product a temporary, but harmless, darkening
of the stool and/or tongue may occur

Stop use and ask a doctor if
■ diarrhea lasts more than 2 days
■ symptoms get worse or last more than 2 days
■ ringing in the ears or loss of hearing occurs

PREGNANCY OR BREAST FEEDING

If pregnant or breast feeding, ask health professional before use.

Keep out of reach of children. In case of overdose, get medical
help or contact a Poison Control Center right away.

DOSAGE AND ADMINISTRATION

Directions ■ Shake well before use
■ use dose cup or tablespoon (TBSP)
■ adults and children 12 years and over: 1 dose (30 mL or 2
TBSP) every 1 hour as needed
■ do not exceed 4 doses (120 mL or 8 TBSP) in 24 hours
■ use until diarrhea stops but not more than 2 days
■ children under 12 years: ask a doctor
■ drink plenty of clear fluids to help prevent dehydration caused by diarrhea

Other information
■ each 30 mL dose cup contains: sodium 13 mg, salicylate 455 mg ■ protect
from freezing ■ avoid excessive heat (over 104°F or 40°C) ■ low sodium

INACTIVE INGREDIENT

Inactive ingredients benzoic acid, D&C red #22, D&C red #28,
flavor, purified water, saccharin sodium, salicylic acid, sodium salicylate, xantham gum

Marc's Product Label

NDC 68998-558-28 * Compare to the active

ingredients in Pepto-BismolTM

Maximum Strength

Marc's

ULTRA STRENGTH

Stomach Relief

Antidiarrheal / Upset Stomach Reliever
Bismuth subsalicylate

5 Symptoms Relief of

• Nausea • Upset Stomach•

• Heartburn • Diarrhea

• Indigestion

12 FL OZ (354 mL)

TAMPER EVIDENT: Do not use if imprinted shrinkband is
missing or broken

*Thls product is not manufactured or dlstnbuted by Procter & Gamble, Inc"
distributor of Pepto BismolTM

Distributed by: LR-144
Marc Glassman, Inc.
West 130th Street
Cleveland, OH 44130

Lot.
Exp.

res